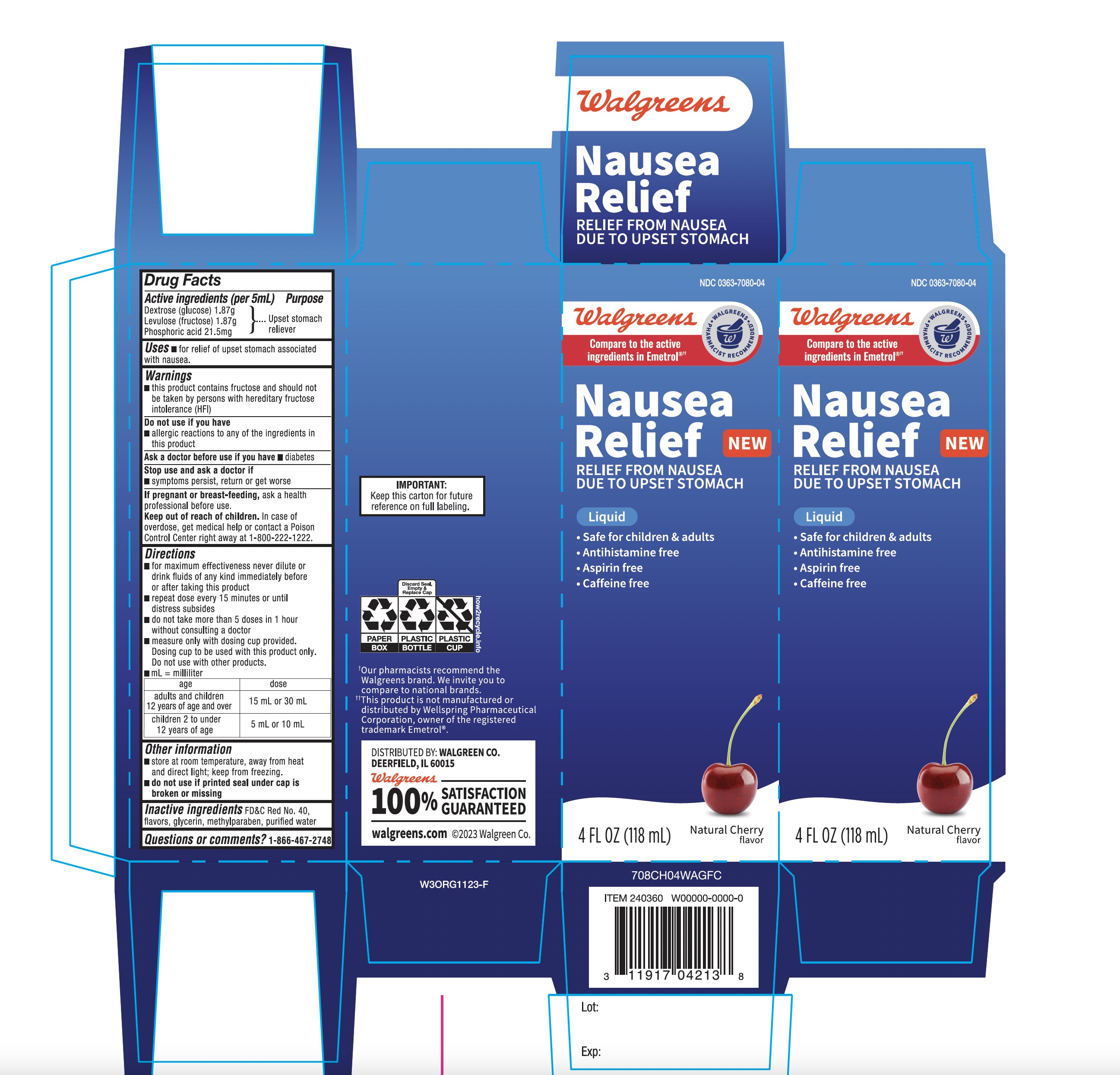 DRUG LABEL: Walgreen Anti Nausea

NDC: 0363-7080 | Form: SOLUTION
Manufacturer: WALGREENS CO.
Category: otc | Type: HUMAN OTC DRUG LABEL
Date: 20251201

ACTIVE INGREDIENTS: DEXTROSE, UNSPECIFIED FORM 1.87 g/5 mL; FRUCTOSE 1.87 g/5 mL; PHOSPHORIC ACID 21.5 mg/5 mL
INACTIVE INGREDIENTS: FD&C RED NO. 40; WATER; GLYCERIN; METHYLPARABEN

Walgreen Anti-Nausea Liquid Relief 4 FL Cherry Flavor

Active ingredients (per 5mL)

Dextrose (glucose) 1.87g

Levulose (fructose) 1.87g

Phosphoric acid 21.5mg

Purpose

Upset Stomach Reliever

Uses

- for relief of upset stomach associated with nausea

Warnings

- This product contains fructose and should not be taken by persons with hereditary fructose intolerance (HFI).

Do not use if you have

- allergic reactions to any of the ingredients in this product

Ask a doctor before use if you have

- diabetes

Stop use and ask a doctor if

- symptoms persist, return or get worse

If pregnant or breast-feeding,

ask a health professional before use.

Keep out of reach of children.

In case of overdose, get medical help or contact a Poison Control Center right away. (1-800-222-1222)

Directions

- for maximum effectiveness never dilute or drink fluids of any kind immediately before or after taking this product
- repeat dose every 15 minutes or until distress subsides
- do not take more than 5 doses in 1 hour without consulting a doctor
- measure only with dosing cup provided. Dosing cup to be used with product only. Do not use with other products.
- mL = milliliters

Age | Dose
Adults and children 12 years of age and over | 15 mL or 30 mL
Children 2 to under 12 years of age | 5 mL or 10 mL

Other information

- Store at room temperature, away from heat and direct light; keep from freezing
- Do not use if printed seal under cap is broken or missing

Inactive ingredients

FD&C red no. 40, flavors, glycerin, methylparaben, and purified water.

Questions or Comments?

1-866-467-2748